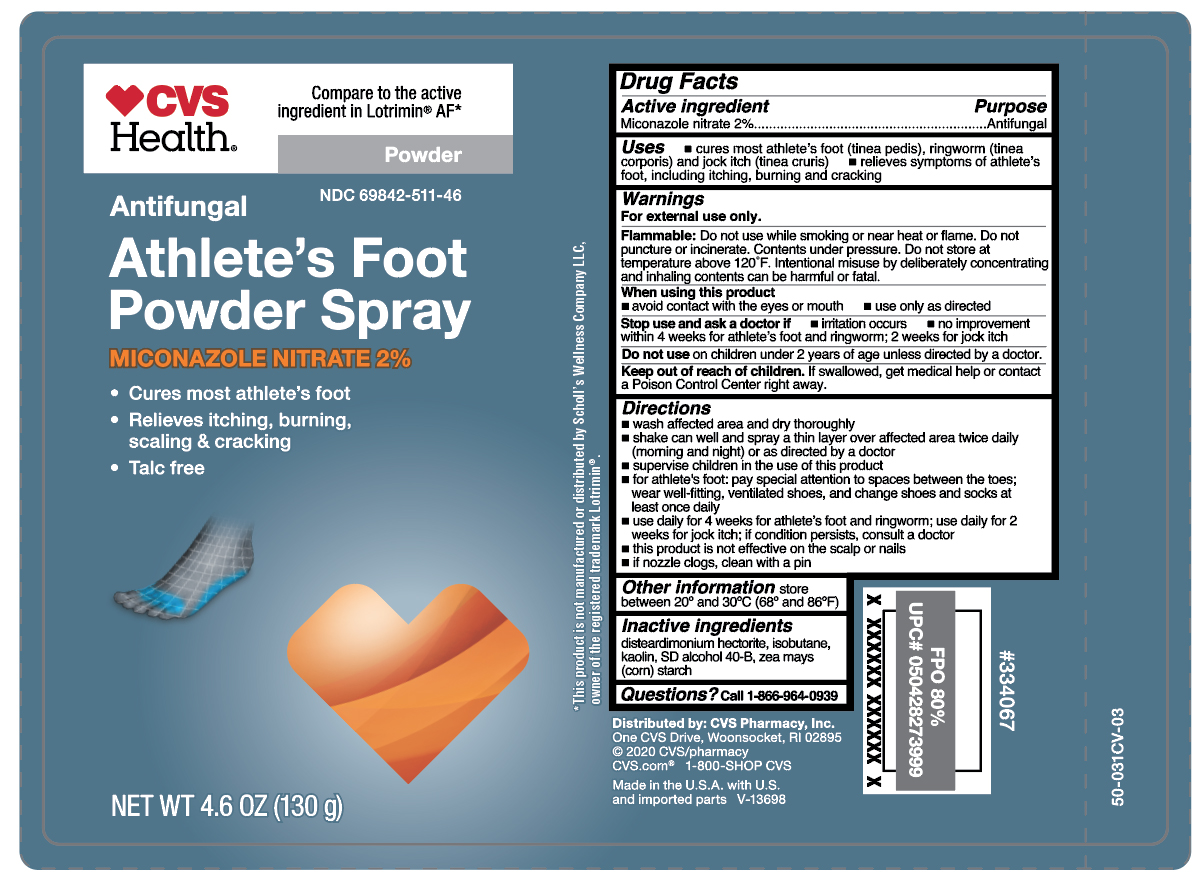 DRUG LABEL: Miconazole Nitrate
NDC: 69842-511 | Form: AEROSOL, POWDER
Manufacturer: CVS Pharmacy
Category: otc | Type: HUMAN OTC DRUG LABEL
Date: 20260218

ACTIVE INGREDIENTS: MICONAZOLE NITRATE 2.6 g/130 g
INACTIVE INGREDIENTS: DISTEARDIMONIUM HECTORITE; ISOBUTANE; KAOLIN; ALCOHOL; ZEA MAYS SUBSP. MAYS WHOLE

CVS Miconazole Athlete's Foot Powder Spray - Talc Free

Active ingredient

Miconazole nitrate 2%

Purpose

Antifungal

Uses

- cures most athlete's foot (tinea pedis), ringworm (tinea corporis) and jock itch (tinea cruris)
- relieves symptoms of athlete's foot, including itching, burning and cracking

Warnings

For external use only.

Flammable:

Do not use while smoking or near heat or flame. Do not puncture or incinerate. Contents under pressure. Do not store at temperature above 120ºF. Intentional misuse by deliberately concentrating and inhaling contents can be harmful or fatal.

When using this product

- avoid contact with the eyes or mouth
- use only as directed

Stop use and ask a doctor if

- irritation occurs
- no improvement within 4 weeks for athlete's foot and ringworm; 2 weeks for jock itch

Do not use

on children under 2 years of age unless directed by a doctor.

Keep out of reach of children.

If swallowed, get medical help or contact a Poison Control Center right away.

Directions

- wash affected area and dry thoroughly
- shake can well and spray a thin layer over affected area twice daily (morning and night) or as directed by a doctor
- supervise children in the use of this product
- for athlete's foot: pay special attention to spaces between the toes; wear well-fitting, ventilated shoes, and change shoes and socks at least once daily
- use daily for 4 weeks for athlete's foot and ringworm; use daily for 2 weeks for jock itch; if conditions persist, consult a doctor
- this product is not effective on the scalp or nails
- if nozzle clogs, clean with a pin

Other information

store between 20º and 30ºC (68ºF and 86º)

Inactive ingredients

disteardimonium hectorite, isobutane, kaolin, SD alcohol 40-B, zea mays (corn) starch

Questions?

Call 1-866-964-0939

Principal Display Panel

CVS

Health

Antifungal

Athlete's Foot

Powder Spray

MICONAZOLE NITRATE 2%

- Cures most athlete's foot
- Relieves itching, burning,

scaling & cracking

- Talc free

NET WT 4.6 OZ (130 g)